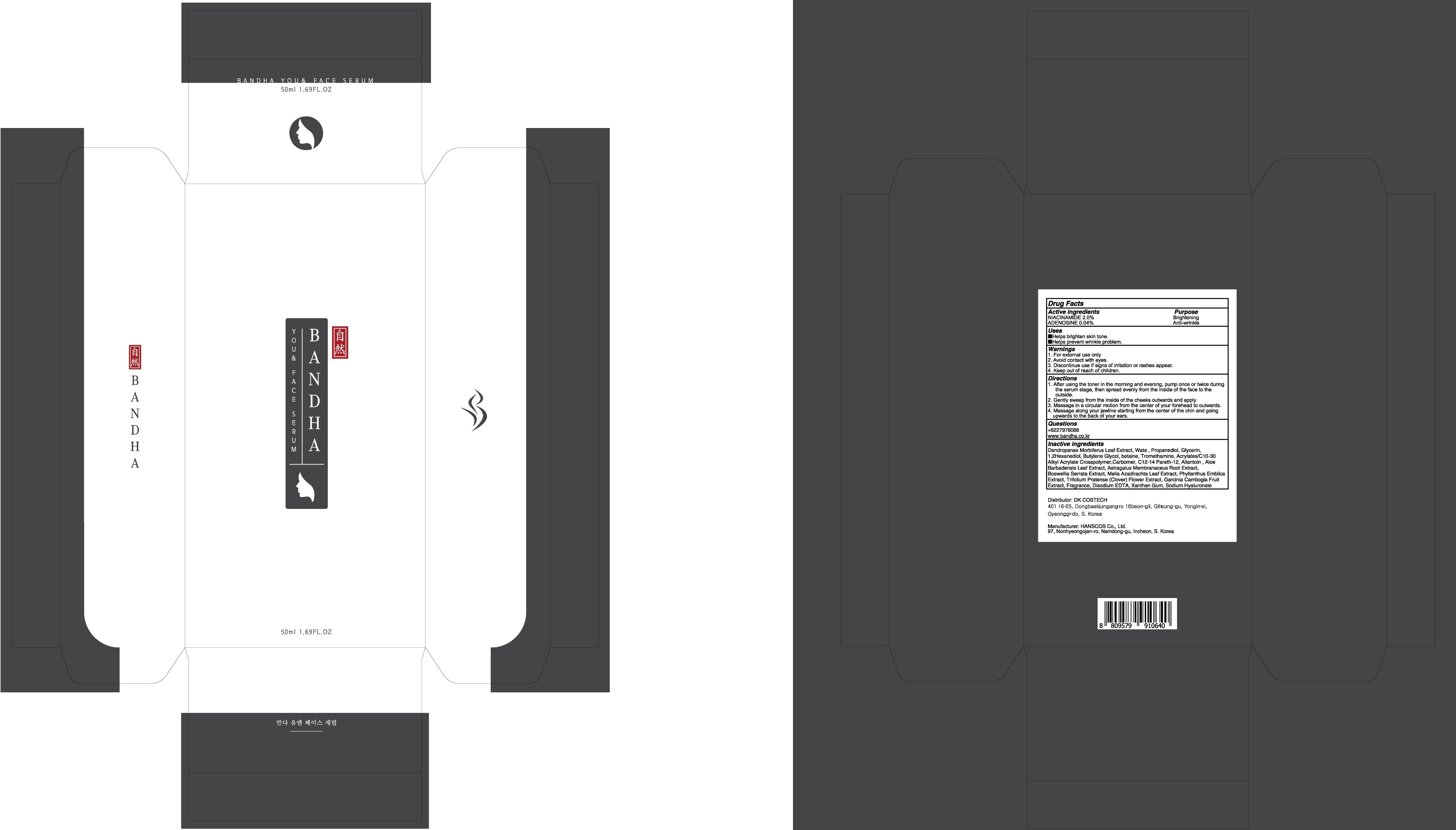 DRUG LABEL: BANDHA YOU AND FACE SERUM
NDC: 80623-020 | Form: LIQUID
Manufacturer: DKCOSTECH
Category: otc | Type: HUMAN OTC DRUG LABEL
Date: 20200923

ACTIVE INGREDIENTS: NIACINAMIDE 1.0 g/50 mL; ADENOSINE 0.02 g/50 mL
INACTIVE INGREDIENTS: Water; Propanediol; Glycerin

ACTIVE INGREDIENTS

NIACINAMIDE 2.0%
ADENOSINE 0.04%

INACTIVE INGREDIENTS

Dendropanax Morbiferus Leaf Extract, Water, Propanediol, Glycerin, 1,2Hexanediol, Butylene Glycol, betaine, Tromethamine, Acrylates/C10-30 Alkyl Acrylate Crosspolymer,Carbomer, C12-14 Pareth-12, Allantoin , Aloe Barbadensis Leaf Extract, Astragalus Membranaceus Root Extract,
Boswellia Serrata Extract, Melia Azadirachta Leaf Extract, Phyllanthus Emblica Extract, Trifolium Pratense (Clover) Flower Extract, Garcinia Cambogia Fruit Extract, Fragrance, Disodium EDTA, Xanthan Gum, Sodium Hyaluronate

PURPOSE

Brightening
Anti-wrinkle

WARNINGS

1. For external use only
2. Avoid contact with eyes.
3. Discontinue use if signs of irritation or rashes appear.
4. Keep out of reach of children.

KEEP OUT OF REACH OF CHILDREN

Uses

■ Helps brighten skin tone.
■ Helps prevent wrinkle problem.

Directions

1. After using the toner in the morning and evening, pump once or twice during the serum stage, then spread evenly from the inside of the face to the outside.
2. Gently sweep from the inside of the cheeks outwards and apply.
3. Massage in a circular motion from the center of your forehead to outwards.
4. Massage along your jawline starting from the center of the chin and going upwards to the back of your ears.

QUESTIONS

+8227978088
www.bandha.co.kr